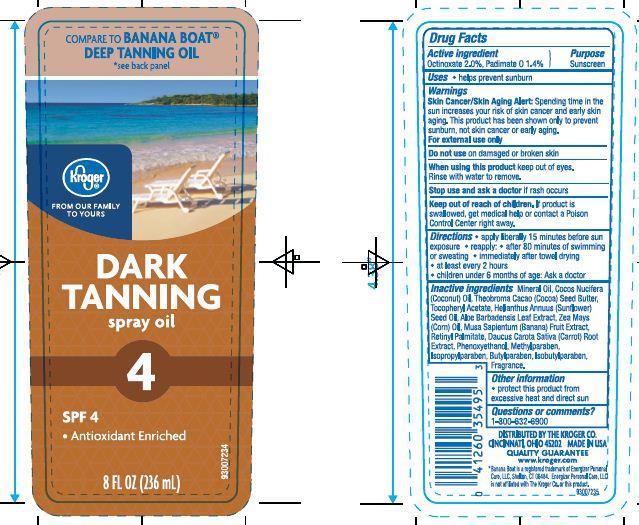 DRUG LABEL: KROGER SPF 4 TANNING OIL
NDC: 30142-929 | Form: SPRAY
Manufacturer: THE KROGER CO
Category: otc | Type: HUMAN OTC DRUG LABEL
Date: 20130814

ACTIVE INGREDIENTS: OCTINOXATE 2 g/100 g; PADIMATE O 1.4 g/100 g
INACTIVE INGREDIENTS: MINERAL OIL; COCONUT OIL; COCOA BUTTER; .ALPHA.-TOCOPHEROL ACETATE; SUNFLOWER OIL; ALOE VERA LEAF; CORN OIL; BANANA; VITAMIN A PALMITATE; CARROT; PHENOXYETHANOL; METHYLPARABEN; ISOPROPYLPARABEN; BUTYLPARABEN; ISOBUTYLPARABEN

Drug Facts

Active ingredients

Octinoxate 2.0%

Padimate O 1.4%

Purpose

Sunscreen

Uses

- helps prevent sunburn

Warnings

Skin Cancer Skin Aging Alert: Spending time in the sun increases your risk of skin cancer and early skin aging. This product has been shown only to prevent sunburn, not skin cancer or early aging.

For external use only

Do not use on damaged or broken skin

When using this product

- keep out of eyes. Rinse with water to remove.

Stop use and ask a doctor

- if rash occurs

Keep out of reach of children

If swallowed, get medical help or contact a Poison Control Center right away.

Directions

- apply liberally 15 minutes before sun exposure
- reapply
- after 80 minutes of swimming or sweating
- immediately after towel drying
- at least every 2 hours
- children under 6 months of age: ask a doctor

Inactive ingredients

Mineral Oil, Cocos Nucifera (Coconut) Oil, Theobroma Cacao (Cocoa) Seed Butter, Tocopheryl Acetate, Helianthus Annuus (Sunflower) Seed Oil, Aloe Barbadensis Leaf Extract, Zea Mays (Corn) Oil, Musa Sapientum (Banana) Fruit Extract, Retinyl Palmitate, Daucus Carota Sativa (Carrot) Root Extract, Phenoxyethanol, Methylparaben, Isopropylparaben, Butylparaben, Isobutylparaben, Fragrance.

Other Information

- protect this product from excessive heat and direct sun

Principal Display Panel

COMPARE TO BANANA BOAT

DEEP TANNING OIL

see back panel

Kroger

FROM OUR FAMILY TO YOURS

DARK TANNING

spray oil

4

SPF 4

- Antioxidant Enriched

8 FL OZ (236 mL)

Questions or comments?

1-800-632-6900